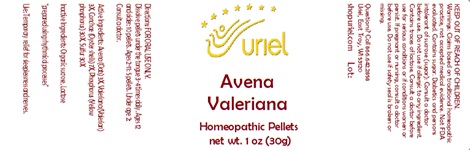 DRUG LABEL: Avena Valeriana
NDC: 48951-1279 | Form: PELLET
Manufacturer: Uriel Pharmacy Inc
Category: homeopathic | Type: HUMAN OTC DRUG LABEL
Date: 20240513

ACTIVE INGREDIENTS: AVENA SATIVA FLOWERING TOP 3 [hp_X]/1 1; VALERIAN 3 [hp_X]/1 1; OSTREA EDULIS SHELL 7 [hp_X]/1 1; PHOSPHORUS 30 [hp_X]/1 1; SULFUR 30 [hp_X]/1 1
INACTIVE INGREDIENTS: SUCROSE; LACTOSE

Avena Valeriana

INDICATIONS AND USAGE

Directions: FOR ORAL USE ONLY.

DOSAGE AND ADMINISTRATION

Dissolve pellets under the tongue 3-4 times daily. Ages 12 and older: 10 pellets. Ages 2-11: 5 pellets. Under age 2: Consult a doctor.

ACTIVE INGREDIENT

Active Ingredients: Avena (Oats) 3X, Valeriana (Valerian) 3X, Conchae (Oyster shells) 7X, Phosphorus (Yellow phosphorus) 30X, Sulfur 30X

Inactive Ingredients: Organic sucrose, Lactose

"prepared using rhythmical processes"

PURPOSE

Use: Temporary relief for sleeplessness and nerves.

KEEP OUT OF REACH OF CHILDREN.

Questions? Call 866.642.2858
Uriel, East Troy, WI 53120
shopuriel.com Lot:

WARNINGS

Warnings: Claims based on traditional homeopathic practice, not accepted medical evidence. Not FDA evaluated. Contains sugar. Diabetics and persons intolerant of sucrose (sugar): Consult a doctor before use. Do not use if allergic to any ingredient. Contains traces of lactose. Consult a doctor before use for serious conditions or if conditions worsen or persist. If pregnant or nursing, consult a doctor before use. Do not use if safety seal is broken or missing.